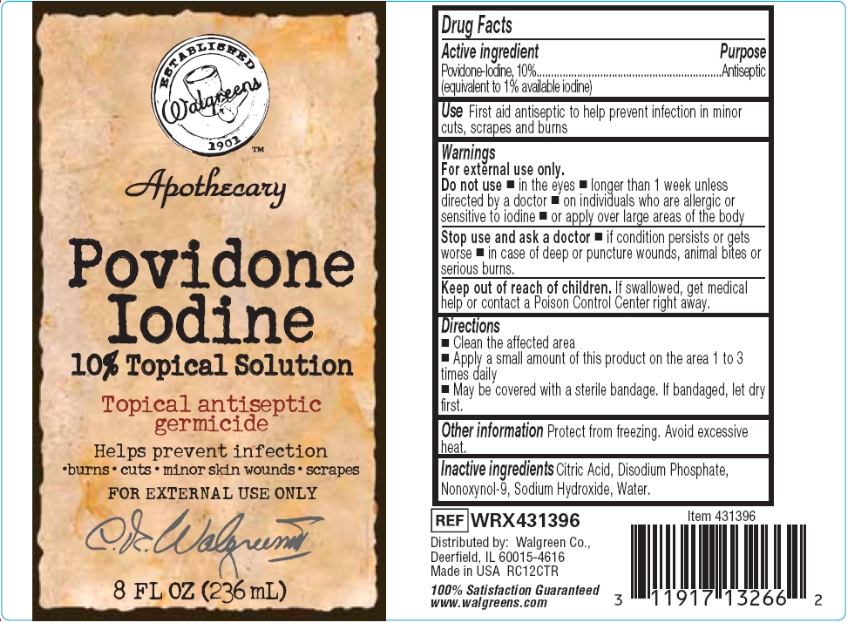 DRUG LABEL: Apothecary PVP Topical
NDC: 0363-0939 | Form: SOLUTION
Manufacturer: Walgreen Company
Category: otc | Type: HUMAN OTC DRUG LABEL
Date: 20160212

ACTIVE INGREDIENTS: POVIDONE-IODINE 1 g/100 mL
INACTIVE INGREDIENTS: CITRIC ACID MONOHYDRATE; SODIUM PHOSPHATE, DIBASIC, DIHYDRATE; NONOXYNOL-9; SODIUM HYDROXIDE; WATER

Drug Facts

Active ingredient

Povidone-Iodine, 10% (equivalent to 1% available iodine)

Purpose

Antiseptic

Uses

First aid antiseptic to help prevent infection in minor cuts, scrapes and burns

Warnings

For external use only.

Do not use

- in the eyes
- longer than one week unless directed by a doctor
- on individuals who are allergic or sensitive to iodine
- or apply over large areas of the body

Stop use and ask a doctor

- if irritation and redness develop
- if condition persists for more than 72 hours
- in case of deep or puncture wounds, animal bites or serious burns.

Keep out of reach of children.

If swallowed, get medical help or contact a Poison Control Center right away.

Directions

- Clean the affected area.
- Apply a small amount of this product on the area 1 to 3 times daily
- May be covered with a sterile bandage. If bandaged, let dry first.

Other Information

Protect from freezing. Avoid excessive heat.

Inactive ingredients

Citric Acid, Disodium Phosphate, Nonoxynol-9, Sodium Hydroxide, Water.

Package/Label Principal Display Panel

Walgreens

Apothecary

Povidone Iodine

10% Topical Solution

Topical antiseptic germicide

Helps prevent infection

- burns
- cuts
- minor skin wounds
- scrapes

FOR EXTERNAL USE ONLY

8 FL OZ (236 mL)